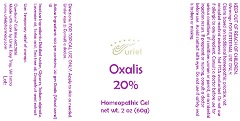 DRUG LABEL: Oxalis 20
NDC: 48951-7180 | Form: GEL
Manufacturer: Uriel Pharmacy Inc.
Category: homeopathic | Type: HUMAN OTC DRUG LABEL
Date: 20190211

ACTIVE INGREDIENTS: OXALIS ACETOSELLA LEAF 1 [hp_X]/1 g
INACTIVE INGREDIENTS: WATER; GLYCERIN; SODIUM ALGINATE; LAVENDER OIL; SORBIC ACID; CITRUS PARADISI SEED; TEA TREE OIL

Oxalis 20

INDICATIONS AND USAGE

Directions: FOR TOPICAL USE ONLY.

DOSAGE AND ADMINISTRATION

Apply to skin as needed. Under age 2: Consult a doctor.

Active Ingredient: 100 gm contains: 20 gm Oxalis (Wood sorrel) 1X

INACTIVE INGREDIENT

Inactive Ingredients: Distilled water, Glycerin, Sodium alginate, Lavender oil, Sorbic acid, Tea tree oil, Grapefruit seed extract

PURPOSE

Use: Temporary relief of cramps.

KEEP OUT OF REACH OF CHILDREN.

Warnings: FOR EXTERNAL USE ONLY.
Claims based on traditional homeopathic practice, not accepted medical evidence. Not FDA evaluated. Do not use if allergic to any ingredient. Consult a doctor before use for serious conditions, if conditions worsen or persist, or accidental ingestion occurs. If pregnant or nursing, consult a doctor before use. Avoid contact with eyes. Do not use if safety seal is broken or missing.

QUESTIONS

Questions? Call 866.642.2858 Made with care by Uriel, Easy Troy, WI 53120 www.urielpharmacy.com